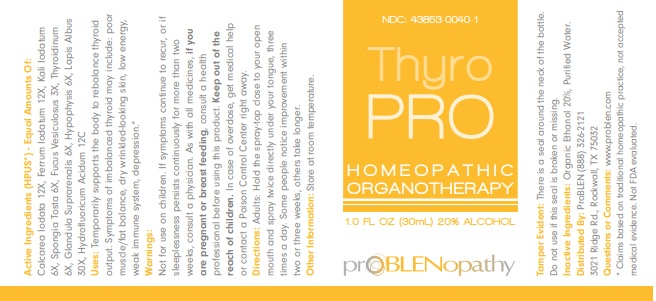 DRUG LABEL: THYROPRO
NDC: 43853-0040 | Form: LIQUID
Manufacturer: ProBlen
Category: homeopathic | Type: HUMAN OTC DRUG LABEL
Date: 20221130

ACTIVE INGREDIENTS: SUS SCROFA PITUITARY GLAND 6 [hp_X]/30 mL; CALCIUM HEXAFLUOROSILICATE 30 [hp_X]/30 mL; HYDROFLUORIC ACID 12 [hp_C]/30 mL; CALCIUM IODIDE 12 [hp_X]/30 mL; FERROUS IODIDE 12 [hp_X]/30 mL; POTASSIUM IODIDE 6 [hp_X]/30 mL; SPONGIA OFFICINALIS SKELETON, ROASTED 6 [hp_X]/30 mL; FUCUS VESICULOSUS 3 [hp_X]/30 mL; THYROID, UNSPECIFIED 6 [hp_X]/30 mL; SUS SCROFA ADRENAL GLAND 6 [hp_X]/30 mL
INACTIVE INGREDIENTS: WATER; ALCOHOL

ThyroPRO

ACTIVE INGREDIENT

Active Ingredients (HPUS*) - Equal Amounts Of: Calcarea Iodata 12X, Ferrum Iodatum 12X, Kali Iodatum 6X, Spongia Tosta 6X, Fucus Vesiculosus 3X, Thyroidinum 6X, Glandula Suprarenalis 6X, Hypophysis 6X, Lapis Albus 30X, Hydrofluoricum Acidum 12C.

* Claims based on traditional homeopathic practice, not accepted medical evidence. Not FDA evaluated.

INDICATIONS AND USAGE

Uses: Temporarily supports the body to rebalance thyroid output. Symptoms of imbalanced thyroid may include: poor muscle/fat balance, dry wrinkled-looking skin, low energy, weak immune system, depression.*

WARNINGS

Warnings: Not for use on children. If symptoms continue to recur, or if sleeplessness persists continuously for more than two
weeks, consult a physician. As with all medicines, if you are pregnant or breast feeding, consult a health professional before using this product. Keep out of the reach of children. In case of overdose, get medical help or contact a Poison Control Center right away.

Keep out of reach of children.

DOSAGE AND ADMINISTRATION

Directions: Adults: Hold the spray-top close to your open mouth and spray twice directly under your tongue, three times a day. Some people notice improvement within two or three weeks, others take longer.

Other Information: Store at room temperature

Inactive Ingredients: Organic Ethanol 20%, Purified Water

PACKAGE LABEL

NDC: 43853-0040-1

ThyroPRO

HOMEOPATHIC ORGANOTHERAPY

1.0 FL OZ (30mL) 20% ALCOHOL

prOBLENopathy

PURPOSE

Purpose: Temporarily supports the body to rebalance thyroid output. Symptoms of imbalanced thyroid may include: poor muscle/fat balance, dry wrinkled-looking skin, low energy, weak immune system, depression.*